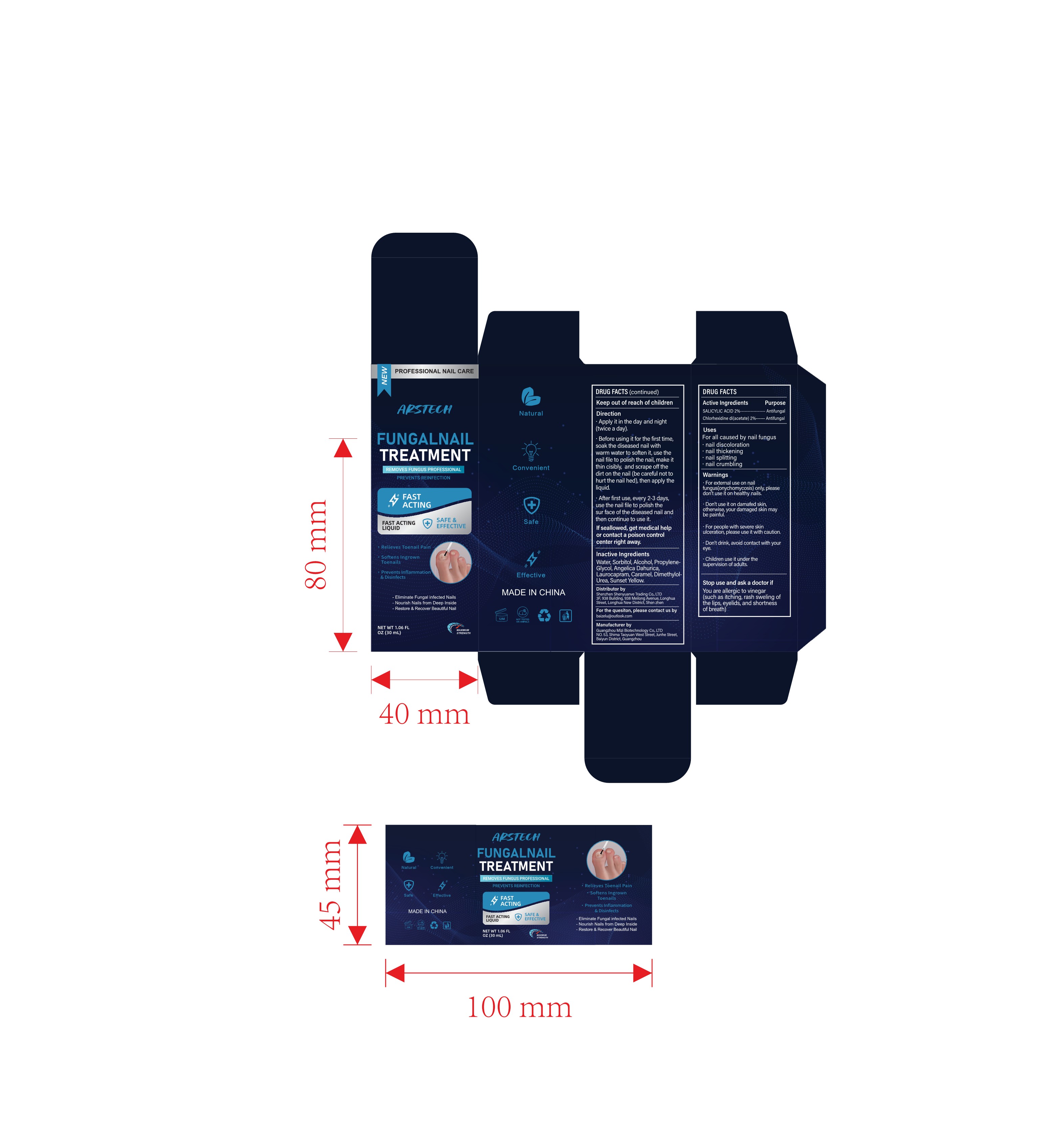 DRUG LABEL: Nail Treatment Liquid
NDC: 84336-002 | Form: LIQUID
Manufacturer: Shenzhen Shenyuanye Trading Co., LTD
Category: otc | Type: HUMAN OTC DRUG LABEL
Date: 20240611

ACTIVE INGREDIENTS: CHLORHEXIDINE ACETATE 2 mg/100 mL; SALICYLIC ACID 2 mg/100 mL
INACTIVE INGREDIENTS: SORBITOL; LAUROCAPRAM; CARAMEL; WATER; OXYMETHUREA; PROPYLENE GLYCOL; FD&C YELLOW NO. 6; ANGELICA DAHURICA ROOT; ALCOHOL

Nail Treatment Liquid

ACTIVE INGREDIENT

SALICYLIC ACID 2%

Chlorhexidine di(acetate) 2%

PURPOSE

REMOVES FUNGUS

INDICATIONS AND USAGE

Uses For all caused by nail fungus

nail discoloration

nail thickening

nail splitting

nail crumbling

WARNINGS

For external use on nailfungus(onychomycosis) only, pleasedon't use it on healthy nails.

DO NOT USE

Don't use it on damafed skin,otherwise, your damaged skin maybe painful.

WHEN USING

Don't drink, avoid contact with your eye.

STOP USE

For people with severe skin ulceration, please use it with caution.

Keep out of reach of children

Children use it under thesupervision of adults.

Stop use and ask a doctor if

You are allergic to vinegar(such as itching, rash sweling ofthe lips, eyelids, and shortnessof breath)

DOSAGE AND ADMINISTRATION

Direction
Apply it in the day and night(twice a day).
Before using it for the first time,soak the diseased nail with warm water to soften it, use thenail file to polish the nail, make itthin cisibly, and scrape off thedirt on the nail (be careful not tohurt the nail hed), then apply theliquid.
After first use, every 2-3 daysuse the nail file to polish thesur face of the diseased nail and then continue to use it.
If seallowed, get medical help or contact a poison controlcenter right away.

INACTIVE INGREDIENT

Water, Sorbitol, Alcohol, Propylene-Glycol, Angelica Dahurica,Laurocapram, Caramel, Dimethylol.Urea, Sunset Yellow.

QUESTIONS

For the quesiton, please contact us bybaizelu@outlook.com